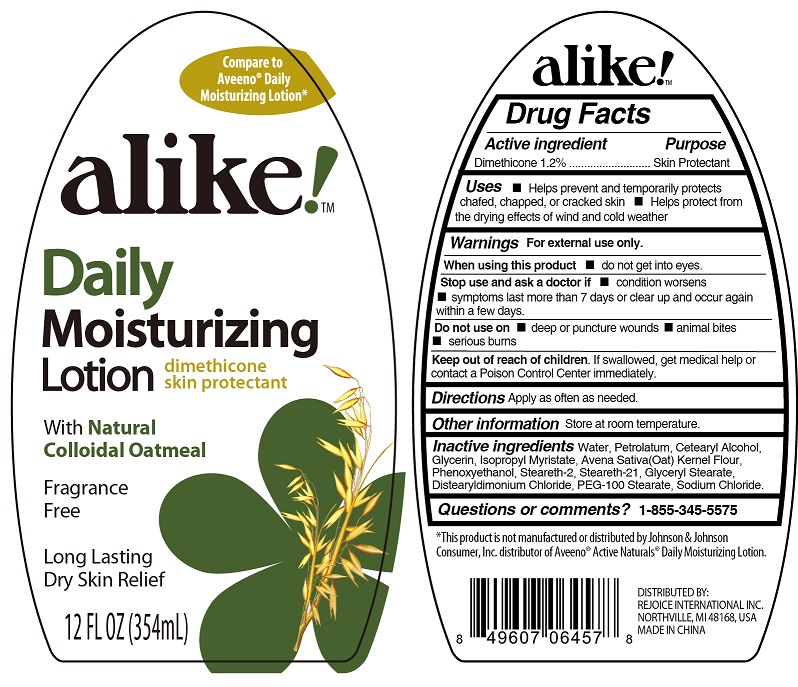 DRUG LABEL: Alike Daily Moisturizing
NDC: 57337-098 | Form: LOTION
Manufacturer: Rejoice International Inc.
Category: otc | Type: HUMAN OTC DRUG LABEL
Date: 20250212

ACTIVE INGREDIENTS: DIMETHICONE 1.2 g/100 mL
INACTIVE INGREDIENTS: PETROLATUM; ISOPROPYL MYRISTATE; OAT KERNEL OIL; PHENOXYETHANOL; STEARETH-2; STEARETH-21; GLYCERYL MONOSTEARATE; PEG-100 STEARATE; WATER; CETOSTEARYL ALCOHOL; GLYCERIN; DISTEARYLDIMONIUM CHLORIDE; SODIUM CHLORIDE

Daily Moisturizing Lotion with Oatmeal 12 oz.

Active ingredient

Dimethicone 1.2%

Purpose

Skin Protectant

Keep out of reach of children. If swallowed, get medical help or contact a Poison Control Center immediately.

Warnings

For external use only

When using this product

- do not get into eyes

Stop use and ask a doctor if

- condition worsens
- symptoms last more than 7 days or clear up and occur again within a few days

Do not use on

- deep or puncture wounds
- animal bites
- serious burns

Directions

Apply as often as needed

INACTIVE INGREDIENT

Water, Petrolatum, Cetearyl Alcohol, Glycerin, Isopropyl Myristate, Avena Sativa (Oat) Kernel Flour, Phenoxyethanol, Steareth-2, Steareth-21, Glycerin Stearate, Distearidimonium Chloride, PEG-100 Stearate, Sodium Chloride

Uses

- Helps prevent and temporarily protects chafed, chapped, or cracked skin
- Helps protect from the drying effects of wind and cold weather